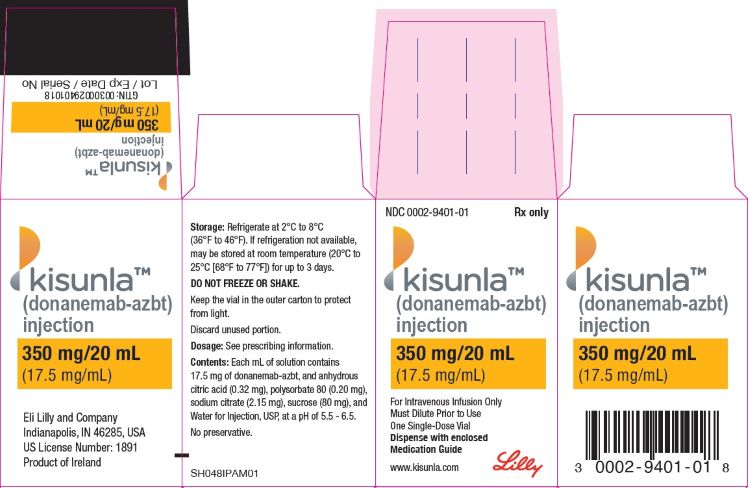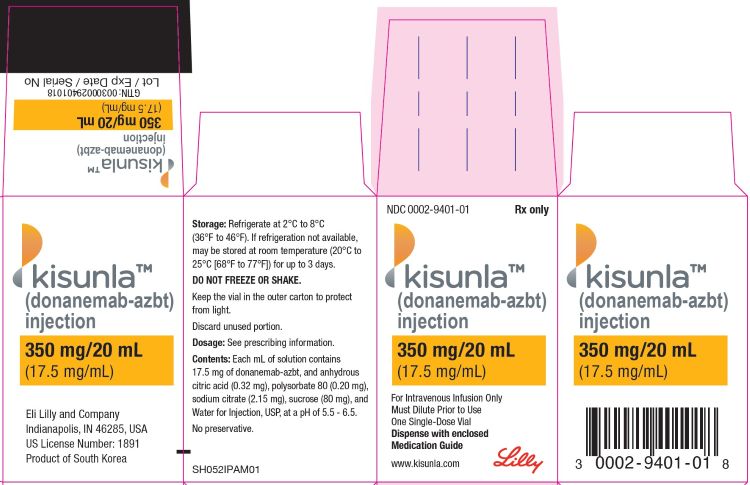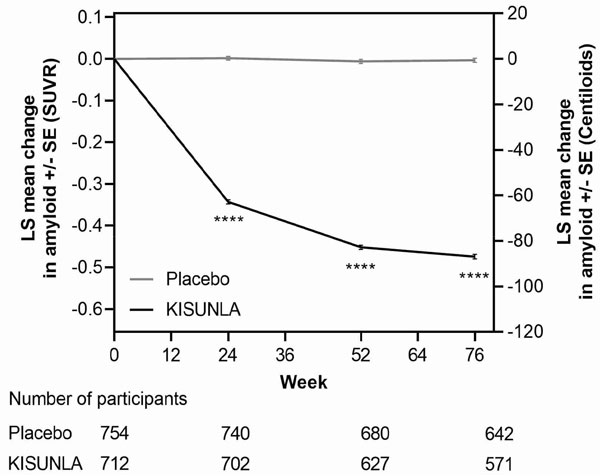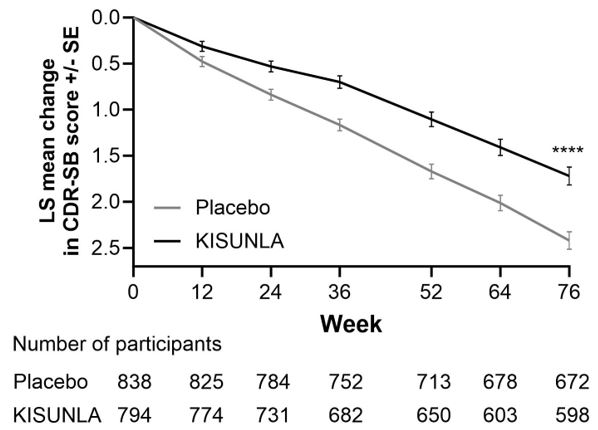 DRUG LABEL: Kisunla
NDC: 0002-9401 | Form: INJECTION, SOLUTION
Manufacturer: Eli Lilly and Company
Category: prescription | Type: HUMAN PRESCRIPTION DRUG LABEL
Date: 20251230

ACTIVE INGREDIENTS: donanemab 17.5 mg/1 mL
INACTIVE INGREDIENTS: sodium citrate, unspecified form 2.15 mg/1 mL; anhydrous citric acid 0.32 mg/1 mL; sucrose 80 mg/1 mL; Polysorbate 80 0.20 mg/1 mL; water

HIGHLIGHTS OF PRESCRIBING INFORMATION

These highlights do not include all the information needed to use KISUNLA safely and effectively. See full prescribing information for KISUNLA.
KISUNLA (donanemab-azbt) injection, for intravenous use
Initial U.S. Approval: 2024

RECENT MAJOR CHANGES

Boxed Warning | 07/2025
Dosage and Administration (2.2, 2.3, 2.4, 2.5) | 07/2025
Warnings and Precautions (5.1, 5.3) | 07/2025

WARNING: AMYLOID RELATED IMAGING ABNORMALITIES

See full prescribing information for complete boxed warning.

Monoclonal antibodies directed against aggregated forms of beta amyloid, including KISUNLA, can cause amyloid related imaging abnormalities (ARIA), as ARIA with edema (ARIA-E) and ARIA with hemosiderin deposition (ARIA-H). ARIA is usually asymptomatic, although serious and life-threatening events can occur. ARIA can be fatal. Serious intracerebral hemorrhages >1 cm have occurred in patients treated with this class of medications. ARIA-E can cause focal neurologic deficits that can mimic ischemic stroke. (5.1, 6.1)

ApoE ε4 Homozygotes

Patients treated with this class of medications, including KISUNLA, who are ApoE ε4 homozygotes have a higher incidence of ARIA, including symptomatic and serious ARIA, compared to heterozygotes and noncarriers. Testing for ApoE ε 4 status should be performed prior to initiation of treatment to inform the risk of developing ARIA. Prior to testing, the risk of ARIA across genotypes and implications of genetic testing results should be discussed with patients. (5.1)

Consider the benefit for the treatment of Alzheimer's disease and risk of ARIA when deciding to treat with KISUNLA. (5.1, 14)

1 INDICATIONS AND USAGE

KISUNLA is an amyloid beta-directed antibody indicated for the treatment of Alzheimer's disease. Treatment with KISUNLA should be initiated in patients with mild cognitive impairment or mild dementia stage of disease, the population in which treatment was initiated in the clinical trials. (1)

2 DOSAGE AND ADMINISTRATION

- Confirm the presence of amyloid beta pathology prior to initiating treatment. (2.1)
- Administer KISUNLA as an intravenous infusion over approximately 30 minutes every four weeks as follows (2.2):
  - Infusion 1: 350 mg
  - Infusion 2: 700 mg
  - Infusion 3: 1,050 mg
  - Infusion 4 and beyond: 1,400 mg
- Consider stopping dosing with KISUNLA based on reduction of amyloid plaques to minimal levels on amyloid PET imaging. (2.2)
- Obtain a recent baseline brain MRI prior to initiating treatment. (2.3, 5.1)
- Obtain an MRI prior to the 2nd, 3rd, 4th, and 7th infusions. If radiographically observed ARIA occurs, treatment recommendations are based on type, severity, and presence of symptoms. (2.3, 5.1)
- Dilution to a final concentration of 4 mg/mL to 10 mg/mL with 0.9% Sodium Chloride Injection, is required prior to administration. (2.4)

3 DOSAGE FORMS AND STRENGTHS

Injection: 350 mg/20 mL (17.5 mg/mL) in a single-dose vial. (3)

4 CONTRAINDICATIONS

KISUNLA is contraindicated in patients with known serious hypersensitivity to donanemab-azbt or to any of the excipients. (4, 5.2)

5 WARNINGS AND PRECAUTIONS

- Amyloid Related Imaging Abnormalities (ARIA): Enhanced clinical vigilance for ARIA is recommended during the first 24 weeks of treatment with KISUNLA. Risk of ARIA, including symptomatic ARIA, was increased in apolipoprotein E ε4 (ApoE ε4) homozygotes compared to heterozygotes and noncarriers. The risk of ARIA-E and ARIA-H is increased in KISUNLA-treated patients with pretreatment microhemorrhages and/or superficial siderosis. If a patient experiences symptoms suggestive of ARIA, clinical evaluation should be performed, including MRI scanning if indicated. (2.3, 5.1)
- Infusion-Related Reactions: The infusion rate may be reduced, or the infusion may be discontinued, and appropriate therapy initiated as clinically indicated. Consider pre-treatment with antihistamines, acetaminophen, or corticosteroids prior to subsequent dosing. (5.3)

6 ADVERSE REACTIONS

Most common adverse reactions (at least 10% and higher incidence compared to placebo): ARIA-E, ARIA-H microhemorrhage, ARIA-H superficial siderosis, and headache. (6.1)

To report SUSPECTED ADVERSE REACTIONS, contact Eli Lilly and Company at 1-800-LillyRx (1-800-545-5979) or FDA at 1-800-FDA-1088 or www.fda.gov/medwatch.

FULL PRESCRIBING INFORMATION

WARNING: AMYLOID RELATED IMAGING ABNORMALITIES

Monoclonal antibodies directed against aggregated forms of beta amyloid, including KISUNLA, can cause amyloid related imaging abnormalities (ARIA), characterized as ARIA with edema (ARIA-E) and ARIA with hemosiderin deposition (ARIA-H). Incidence and timing of ARIA vary among treatments. ARIA usually occurs early in treatment and is usually asymptomatic, although serious and life-threatening events can occur. ARIA can be fatal. Serious intracerebral hemorrhages >1 cm, some of which have been fatal, have been observed in patients treated with this class of medications. Because ARIA-E can cause focal neurologic deficits that can mimic an ischemic stroke, treating clinicians should consider whether such symptoms could be due to ARIA-E before giving thrombolytic therapy in a patient being treated with KISUNLA [see Warnings and Precautions (5.1), Adverse Reactions (6.1)].

ApoE ε4 Homozygotes

Patients who are apolipoprotein E ε4 (ApoE ε4) homozygotes (approximately 15% of Alzheimer's disease patients) treated with this class of medications, including KISUNLA, have a higher incidence of ARIA, including symptomatic, serious, and severe radiographic ARIA, compared to heterozygotes and noncarriers [see Warnings and Precautions (5.1)]. Testing for ApoE ε4 status should be performed prior to initiation of treatment to inform the risk of developing ARIA. Prior to testing, the risk of ARIA across genotypes and the implications of genetic testing results should be discussed with patients. Prescribers should inform patients that if genotype testing is not performed, they can still be treated with KISUNLA; however, it cannot be determined if they are ApoE ε4 homozygotes and at higher risk for ARIA [see Warnings and Precautions (5.1)].

Consider the benefit of KISUNLA for the treatment of Alzheimer's disease and potential risk of serious adverse events associated with ARIA when deciding to initiate treatment with KISUNLA [see Warnings and Precautions (5.1) and Clinical Studies (14)].

1 INDICATIONS AND USAGE

KISUNLATM is indicated for the treatment of Alzheimer's disease. Treatment with KISUNLA should be initiated in patients with mild cognitive impairment or mild dementia stage of disease, the population in which treatment was initiated in the clinical trials.

2 DOSAGE AND ADMINISTRATION

2.1 Patient Selection

Confirm the presence of amyloid beta pathology prior to initiating treatment [see Clinical Pharmacology (12.1)].

2.2 Dosing Instructions

Administer KISUNLA every four weeks as an intravenous infusion over approximately 30 minutes with the recommended dosage and dosing schedule described in Table 1. KISUNLA must be diluted prior to administration (see Table 4).

Table 1: Recommended Dosage* and Dosing Schedule
Intravenous Infusion (every 4 weeks) | KISUNLA Dosage (administered over approximately 30 minutes)
Infusion 1 | 350 mg
Infusion 2 | 700 mg
Infusion 3 | 1,050 mg
Infusion 4 and beyond | 1,400 mg
*Dosing Regimen 2 [see Warnings and Precautions (5.1) and Clinical Studies (14)]

Consider stopping dosing with KISUNLA based on reduction of amyloid plaques to minimal levels on amyloid PET imaging. In Study 1 and Study 2, dosing was stopped based on a reduction of amyloid levels below predefined thresholds on PET imaging [see Clinical Studies (14)].

If an infusion is missed, resume administration every 4 weeks at the same dose as soon as possible.

2.3 Monitoring and Dosing Interruption for Amyloid Related Imaging Abnormalities

KISUNLA can cause amyloid related imaging abnormalities -edema (ARIA-E) and -hemosiderin deposition (ARIA-H) [see Warnings and Precautions (5.1) and Adverse Reactions (6.1)].

Monitoring for ARIA

Obtain a recent baseline brain magnetic resonance imaging (MRI) prior to initiating treatment with KISUNLA. Obtain an MRI prior to the 2nd, 3rd, 4th, and 7th infusions. If a patient experiences symptoms suggestive of ARIA, clinical evaluation should be performed, including an MRI if indicated.

Recommendations for Dosing Interruptions in Patients with ARIA

ARIA-E

The recommendations for dosing interruptions for patients with ARIA-E are provided in Table 2.

Table 2: Dosing Recommendations for Patients With ARIA-Ec
Clinical Symptom Severitya | ARIA-E Severity on MRI
Clinical Symptom Severitya | Mild | Moderate | Severe
Asymptomatic | May continue dosing at current dose and schedule | Suspend dosingb | Suspend dosingb
Mild | May continue dosing based on clinical judgment | Suspend dosingb | Suspend dosingb
Moderate or Severe | Suspend dosingb
a Mild: discomfort noticed, but no disruption of normal daily activity.
Moderate: discomfort sufficient to reduce or affect normal daily activity.
Severe: incapacitating, with inability to work or to perform normal daily activity.
b Suspend until MRI demonstrates radiographic resolution and symptoms, if present, resolve; consider a follow-up MRI to assess for resolution 2 to 4 months after initial identification. Resumption of dosing should be guided by clinical judgment.
c See Table 5 for MRI radiographic severity [Warning and Precautions (5.1)].

ARIA-H

The recommendations for dosing interruptions for patients with ARIA-H are provided in Table 3.

Table 3: Dosing Recommendations for Patients With ARIA-Hc
Clinical Symptom Severity | ARIA-H Severity on MRI
Clinical Symptom Severity | Mild | Moderate | Severe
Asymptomatic | May continue dosing at current dose and schedule | Suspend dosinga | Suspend dosingb
Symptomatic | Suspend dosinga | Suspend dosinga | Suspend dosingb
a Suspend until MRI demonstrates radiographic stabilization and symptoms, if present, resolve; resumption of dosing should be guided by clinical judgment; consider a follow-up MRI to assess for stabilization 2 to 4 months after initial identification.
b Suspend until MRI demonstrates radiographic stabilization and symptoms, if present, resolve. Use clinical judgment when considering whether to continue treatment or permanently discontinue KISUNLA.
c See Table 5 for MRI radiographic severity [Warning and Precautions (5.1)].

In patients who develop intracerebral hemorrhage greater than 1 cm in diameter during treatment with KISUNLA, suspend dosing until MRI demonstrates radiographic stabilization and symptoms, if present, resolve. Use clinical judgment when considering whether to continue treatment or permanently discontinue KISUNLA after radiographic stabilization and resolution of symptoms.

2.4 Dilution Instructions

- Prior to administration, KISUNLA must be diluted with 0.9% sodium chloride injection (see Table 4).
- Use aseptic technique when preparing the diluted KISUNLA solution for intravenous infusion.
- Allow KISUNLA to equilibrate to room temperature before preparation.
- Parenteral drug products should be inspected visually for particulate matter and discoloration prior to administration, whenever solution and container permit. KISUNLA solution is clear to opalescent, colorless to slightly yellow to slightly brown. Do not use if particulate matter or discolorations are present.
- Withdraw required volume of KISUNLA and mix with 0.9% sodium chloride injection, to the recommended total volume for a final concentration of 4 mg/mL to 10 mg/mL (see Table 4). Use only 0.9% sodium chloride injection for dilution.

Table 4: Preparation of KISUNLA
KISUNLA Dose (mg) | KISUNLA Volume (mL) | Volume of 0.9% Sodium Chloride Injection Diluent (mL) | Final Volume of Diluted Solution to be Infused (mL) | Final Concentration of Diluted Solution (mg/mL)a
350 mg | 20 mL | 15 mL to 67.5 mL | 35 mL to 87.5 mL | 350 mg/87.5 mL (4 mg/mL) to 350 mg/35 mL (10 mg/mL)
700 mg | 40 mLb | 30 mL to 135 mL | 70 mL to 175 mL | 700 mg/175 mL (4 mg/mL) to 700 mg/70 mL (10 mg/mL)
1,050 mg | 60 mLc | 45 mL to 202.5 mL | 105 mL to 262.5 mL | 1,050 mg/262.5 mL (4 mg/mL) to 1,050 mg/105 mL (10 mg/mL)
1,400 mg | 80 mLd | 60 mL to 270 mL | 140 mL to 350 mL | 1,400 mg/350 mL (4 mg/mL) to 1,400 mg/140 mL (10 mg/mL)
a final concentration of 4 mg/mL to 10 mg/mL
b 2 vials of KISUNLA
c 3 vials of KISUNLA
d 4 vials of KISUNLA

- Each vial is for one-time use only. Discard any unused portion left in the vial.
- Gently invert the diluted KISUNLA solution to mix completely. Do not shake.
- After dilution, immediate use is recommended [see Description (11)]. If the diluted KISUNLA solution is not administered immediately, store refrigerated at 2°C to 8°C (36°F to 46°F) for up to 72 hours or at room temperature (20°C to 25°C [68°F to 77°F]) for up to 12 hours.
- Do not freeze the diluted KISUNLA solution.
- Storage times include the duration of infusion.

2.5 Administration Instructions

- Visually inspect the diluted KISUNLA solution for particles or discoloration prior to administration. Do not use if it is discolored, or opaque or foreign particles are seen.
- Prior to infusion, if the diluted solution has been stored under refrigeration, allow the diluted KISUNLA solution to warm to room temperature.
- Administer the entire diluted solution intravenously over approximately 30 minutes.
- Flush the line only with 0.9% sodium chloride injection at the end of the infusion per access specific line maintenance protocol.
- Observe the patient post-infusion for a minimum of 30 minutes, and consider longer periods of observation if clinically indicated, to evaluate for infusion reactions and hypersensitivity reactions. The infusion rate may be reduced, or the infusion may be discontinued, and appropriate therapy administered as clinically indicated. Consider pre-medication at subsequent dosing with antihistamines, non-steroidal anti-inflammatory drugs, or corticosteroids [see Warnings and Precautions (5.2)].

3 DOSAGE FORMS AND STRENGTHS

Injection: 350 mg/20 mL (17.5 mg/mL) clear to opalescent, colorless to slightly yellow to slightly brown solution in a single-dose vial.

4 CONTRAINDICATIONS

KISUNLA is contraindicated in patients with known serious hypersensitivity to donanemab-azbt or to any of the excipients. Reactions have included anaphylaxis [see Warnings and Precautions (5.2)].

5 WARNINGS AND PRECAUTIONS

5.1 Amyloid Related Imaging Abnormalities

Monoclonal antibodies directed against aggregated forms of beta amyloid, including KISUNLA, can cause amyloid related imaging abnormalities (ARIA), characterized as ARIA with edema (ARIA-E), which can be observed on MRI as brain edema or sulcal effusions, and ARIA with hemosiderin deposition (ARIA-H), which includes microhemorrhage and superficial siderosis. ARIA can occur spontaneously in patients with Alzheimer's disease, particularly in patients with MRI findings suggestive of cerebral amyloid angiopathy, such as pretreatment microhemorrhage or superficial siderosis. ARIA-H associated with monoclonal antibodies directed against aggregated forms of beta amyloid generally occurs in association with an occurrence of ARIA-E. ARIA-H of any cause and ARIA-E can occur together.

ARIA usually occurs early in treatment and is usually asymptomatic, although serious and life-threatening events, including seizure and status epilepticus, can occur. ARIA can be fatal. When present, reported symptoms associated with ARIA may include, but are not limited to, headache, confusion, visual changes, dizziness, nausea, and gait difficulty. Focal neurologic deficits may also occur. Symptoms associated with ARIA usually resolve over time. In addition to ARIA, intracerebral hemorrhages greater than 1 cm in diameter have occurred in patients treated with KISUNLA.

Consider the benefit of KISUNLA for the treatment of Alzheimer's disease and potential risk of serious adverse events associated with ARIA when deciding to initiate treatment with KISUNLA.

Study 1 and Study 2 Overview [see Clinical Studies (14)]

In Study 1, safety was assessed in patients who received KISUNLA Dosing Regimen 1 (n = 853) compared to those who received placebo (n = 874). In Study 2, the effect of different dosing regimens of KISUNLA on ARIA was assessed, including in patients who received KISUNLA Dosing Regimen 2 (n=212), which is the recommended dosage and described below.

Incidence of ARIA

A lower incidence of ARIA was observed with Dosing Regimen 2 as compared to Dosing Regimen 1. Therefore, Dosing Regimen 2 is the recommended dosage for KISUNLA.

In Study 1, symptomatic ARIA-E occurred in 6% of patients through 18 months of treatment with KISUNLA [see Adverse Reactions (6.1)]. Clinical symptoms associated with ARIA-E resolved in approximately 85% of those patients. Including asymptomatic radiographic events, ARIA, ARIA-E, and ARIA-H were observed in 36%, 24%, and 31% of patients treated with KISUNLA, respectively, compared to 14%, 2%, and 13% of patients on placebo, respectively. There was no increase in isolated ARIA-H (i.e., ARIA-H in patients who did not also experience ARIA-E) for KISUNLA compared to placebo.

In Study 2, symptomatic ARIA-E occurred in 3% of patients and symptomatic ARIA-H occurred in less than 1% of patients through 12 months of treatment with KISUNLA [see Adverse Reactions (6.1)]. Clinical symptoms associated with ARIA-E resolved in approximately 67% of patients at 12 months. Including asymptomatic radiographic events, ARIA, ARIA-E, and ARIA-H were observed in 29%, 16%, and 25% of patients treated with KISUNLA.

Incidence of Intracerebral Hemorrhage

Intracerebral hemorrhage greater than 1 cm in diameter was reported in 0.5% of patients treated with KISUNLA compared to 0.2% of patients on placebo in Study 1, and in 1% of patients treated with KISUNLA in Study 2. Fatal events of intracerebral hemorrhage in patients taking KISUNLA have been observed.

Risk Factors for ARIA and Intracerebral Hemorrhage

ApoE ε4 Carrier Status

The risk of ARIA, including symptomatic and serious ARIA, is increased in apolipoprotein E ε4 (ApoE ε4) homozygotes, which include approximately 15% of Alzheimer's disease patients.

In Study 1, of patients in the KISUNLA arm (n=850), 17% were ApoE ε4 homozygotes, 53% were heterozygotes, and 30% were noncarriers. The incidence of ARIA through 18 months was higher in ApoE ε4 homozygotes (55% on KISUNLA vs. 22% on placebo) than in heterozygotes (36% on KISUNLA vs. 13% on placebo) and noncarriers (25% on KISUNLA vs. 12% on placebo). Among patients treated with KISUNLA, symptomatic ARIA-E occurred in 8% of ApoE ε4 homozygotes compared with 7% of heterozygotes and 4% of noncarriers. Serious events of ARIA occurred in 3% of ApoE ε4 homozygotes, 2% of heterozygotes, and 1% of noncarriers.

In Study 2, of patients treated with KISUNLA Dosing Regimen 2 (n=211), 10% were ApoE ε4 homozygotes, 55% were heterozygotes, and 36% were noncarriers. Symptomatic ARIA-E occurred in 0% of ApoE ε4 homozygotes compared with 4% of heterozygotes and 3% of noncarriers. The small number of events and limited exposure in the ApoE ε4 subgroups limit definitive conclusions about the risk of ARIA-E.

The recommendations for management of ARIA do not differ based on ApoE ε4 carrier status [see Dosage and Administration (2.3)]. Testing for ApoE ε4 status should be performed prior to initiation of treatment to inform the risk of developing ARIA. Prior to testing, prescribers should discuss with patients the risk of ARIA across genotypes and the implications of genetic testing results. Prescribers should inform patients that if genotype testing is not performed, they can still be treated with KISUNLA; however, it cannot be determined if they are ApoE ε4 homozygotes and at a higher risk for ARIA. An FDA-authorized test for detection of ApoE ε4 alleles to identify patients at risk of ARIA if treated with KISUNLA is not currently available. Currently available tests used to identify ApoE ε4 alleles may vary in accuracy and design.

Radiographic Findings of Cerebral Amyloid Angiopathy (CAA)

Neuroimaging findings that may indicate CAA include evidence of prior intracerebral hemorrhage, cerebral microhemorrhage, and cortical superficial siderosis. CAA has an increased risk for intracerebral hemorrhage. The presence of an ApoE ε4 allele is also associated with cerebral amyloid angiopathy.

In Study 1, the baseline presence of at least 2 microhemorrhages or the presence of at least 1 area of superficial siderosis on MRI, which may be suggestive of CAA, were identified as risk factors for ARIA. Patients were excluded from enrollment in Study 1 for findings on neuroimaging of prior intracerebral hemorrhage greater than 1 cm in diameter, more than 4 microhemorrhages, more than 1 area of superficial siderosis, severe white matter disease, and vasogenic edema.

Concomitant Antithrombotic or Thrombolytic Medication

In Study 1, baseline use of antithrombotic medication (aspirin, other antiplatelets, or anticoagulants) was allowed. The majority of exposures to antithrombotic medications were to aspirin. The incidence of ARIA-H was 30% (106/349) in patients taking KISUNLA with a concomitant antithrombotic medication within 30 days compared to 29% (148/504) who did not receive an antithrombotic within 30 days of an ARIA-H event. The incidence of intracerebral hemorrhage greater than 1 cm in diameter was 0.6% (2/349 patients) in patients taking KISUNLA with a concomitant antithrombotic medication compared to 0.4% (2/504) in those who did not receive an antithrombotic. The number of events and the limited exposure to non-aspirin antithrombotic medications limit definitive conclusions about the risk of ARIA or intracerebral hemorrhage in patients taking antithrombotic medications.

One fatal intracerebral hemorrhage occurred in a patient taking KISUNLA in the setting of focal neurologic symptoms of ARIA and the use of a thrombolytic agent in Study 1, and one fatal intracerebral hemorrhage occurred in the setting of ARIA and the use of a thrombolytic agent in Study 2. Additional caution should be exercised when considering the administration of antithrombotics or a thrombolytic agent (e.g., tissue plasminogen activator) to a patient already being treated with KISUNLA. Because ARIA-E can cause focal neurologic deficits that can mimic an ischemic stroke, treating clinicians should consider whether such symptoms could be due to ARIA-E before giving thrombolytic therapy in a patient being treated with KISUNLA.

Caution should be exercised when considering the use of KISUNLA in patients with factors that indicate an increased risk for intracerebral hemorrhage and in particular for patients who need to be on anticoagulant therapy or patients with findings on MRI that are suggestive of cerebral amyloid angiopathy.

Radiographic Severity

The radiographic severity of ARIA associated with KISUNLA was classified by the criteria shown in Table 5.

Table 5: ARIA MRI Classification Criteria
ARIA Type | Radiographic Severity
ARIA Type | Mild | Moderate | Severe
ARIA-E | FLAIR hyperintensity confined to sulcus and/or cortex/subcortex white matter in one location <5 cm. | FLAIR hyperintensity 5 to 10 cm in single greatest dimension, or more than 1 site of involvement, each measuring <10 cm. | FLAIR hyperintensity >10 cm with associated gyral swelling and sulcal effacement. One or more separate/independent sites of involvement may be noted.
ARIA-H microhemorrhage | Less than or equal to 4 new incident microhemorrhages | 5 to 9 new incident microhemorrhages | 10 or more new incident microhemorrhages
ARIA-H superficial siderosis | 1 newa focal area of superficial siderosis | 2 new focal areas of superficial siderosis | Greater than 2 new focal areas of superficial siderosis
a Includes new or worsening superficial siderosis.

In Study 1, the majority of ARIA-E radiographic events occurred early in treatment (within the first 24 weeks), although ARIA can occur at any time and patients can have more than one episode. Resolution on MRI after the first ARIA-E event occurred in 63% of patients treated with KISUNLA by 12 weeks, 80% by 20 weeks, and 83% overall after detection. Among patients treated with KISUNLA, the rate of severe radiographic ARIA-E was highest in ApoE ε4 homozygotes (n=143) compared to heterozygotes (n=452) or noncarriers (n=255) at rates of 3%, 2%, and 0.4%, respectively. Among patients treated with KISUNLA, the rate of severe radiographic ARIA-H was highest in ApoE ε4 homozygotes (n=143) compared to heterozygotes (n=452) or noncarriers (n=255) at rates of 22%, 8%, and 4%, respectively.

Table 6 shows the maximum radiographic severity for ARIA-E, ARIA-H microhemorrhage, and ARIA-H superficial siderosis in Study 1 and Study 2.

Table 6: Maximum Radiographic Severity in Patients Treated with KISUNLA in Study 1 Study 2
 | Study 1 Dosing Regimen 1 N=853 % |  |  | Study 2 Dosing Regimen 2 N=212 %
 | Mild | Moderate | Severe | Mild | Moderate | Severe
ARIA-E | 7 | 15 | 2 | 6 | 9 | 0
ARIA-H microhemorrhage | 17 | 4 | 5 | 17 | 3 | 2
ARIA-H superficial siderosis | 6 | 4 | 5 | 4 | 3 | 1
*Administered as Dosing Regimen 2 over 12 months of treatment

Monitoring and Dose Management Guidelines

Recommendations for dosing in patients with ARIA-E depend on clinical symptoms and radiographic severity [see Dosage and Administration (2.3)]. Recommendations for dosing in patients with ARIA-H depend on the type of ARIA-H and radiographic severity [see Dosage and Administration (2.3)]. Use clinical judgment in considering whether to continue dosing in patients with recurrent ARIA-E.

Baseline brain MRI and periodic monitoring with MRI are recommended [see Dosage and Administration (2.3)]. Enhanced clinical vigilance for ARIA is recommended during the first 24 weeks of treatment with KISUNLA. If a patient experiences symptoms suggestive of ARIA, clinical evaluation should be performed, including MRI if indicated. If ARIA is observed on MRI, careful clinical evaluation should be performed prior to continuing treatment.

There is limited experience in patients who continued dosing through asymptomatic but radiographically mild to moderate ARIA-E. There are limited data for dosing patients who have experienced recurrent episodes of ARIA-E.

Providers should encourage patients to participate in real world data collection (e.g., registries) to help further the understanding of Alzheimer's disease and the impact of Alzheimer's disease treatments. Providers and patients can contact 1-800-LillyRx (1-800-545-5979) for a list of currently enrolling programs.

5.2 Hypersensitivity Reactions

Hypersensitivity reactions, including anaphylaxis and angioedema, have occurred in patients who were treated with KISUNLA [see Adverse Reactions (6.1)]. Promptly discontinue the infusion upon the first observation of any signs or symptoms consistent with a hypersensitivity reaction and initiate appropriate therapy. KISUNLA is contraindicated in patients with a history of serious hypersensitivity to donanemab-azbt or to any of the excipients of KISUNLA.

5.3 Infusion-Related Reactions

In Study 1, infusion-related reactions were observed in 9% of patients treated with KISUNLA, the majority (70%) of which occurred within the first 4 infusions, compared to 0.5% of patients on placebo. Infusion-related reactions were mostly mild (57%) or moderate (39%) in severity. Infusion-related reactions resulted in discontinuations in 4% of patients treated with KISUNLA.

In Study 2, infusion-related reactions associated with KISUNLA occurred in 16% of patients; the majority (88%) occurred within the first 4 infusions. Infusion-related reactions were mostly mild (47%) or moderate (50%) in severity. Infusion-related reactions resulted in discontinuations in 2.8% of patients treated with KISUNLA.

Most infusion-related reactions associated with KISUNLA occurred during the infusion or within 30 minutes after completion of the infusion, however some have occurred hours after an infusion. Signs and symptoms of infusion-related reactions include chills, erythema, nausea/vomiting, flushing, difficulty breathing/dyspnea, sweating, elevated blood pressure, headache, chest pain, and low blood pressure.

In the event of an infusion-related reaction, the infusion rate may be reduced, or the infusion may be discontinued, and appropriate therapy initiated as clinically indicated. Consider pre-treatment with antihistamines, acetaminophen, or corticosteroids prior to subsequent dosing.

6 ADVERSE REACTIONS

The following clinically significant adverse reactions are described elsewhere in the labeling:

- Amyloid Related Imaging Abnormalities [see Warnings and Precautions (5.1)]
- Hypersensitivity Reactions [see Warnings and Precautions (5.2)]
- Infusion-Related Reactions [see Warnings and Precautions (5.3)]

6.1 Clinical Trials Experience

Because clinical trials are conducted under widely varying conditions, adverse reaction rates observed in the clinical trials of a drug cannot be directly compared to rates in the clinical trials of another drug and may not reflect the rates observed in practice.

Dosing Regimen and Safety

A lower incidence of ARIA occurred with the dosing regimen administered in Study 2 (350 mg/700 mg/1,050 mg/1,400 mg; Dosing Regimen 2) as compared to the regimen administered in Study 1 (700 mg/700 mg/700 mg/1,400 mg; Dosing Regimen 1); therefore, Dosing Regimen 2 is recommended for administration of KISUNLA [see Dosage and Administration (2.2), Warnings and Precautions (5.1), Clinical Pharmacology (12.2), Clinical Studies (14)].

The safety of KISUNLA has been evaluated in 3727 patients with Alzheimer's disease who received at least one dose of KISUNLA intravenously. In the other clinical studies of KISUNLA, 1912 patients with Alzheimer's disease received KISUNLA once monthly for at least 6 months, 1057 patients for at least 12 months, and 432 patients for at least 18 months, at the Dosing Regimen 1.

Study 1

In Study 1 (NCT04437511), a total of 853 patients with Alzheimer's disease received at least one dose of KISUNLA; patients were randomized to receive KISUNLA Dosing Regimen 1 or placebo.

Thirteen percent of patients treated with KISUNLA compared to 4% of patients on placebo stopped study treatment because of an adverse reaction. The most common adverse reaction leading to discontinuation of KISUNLA was infusion-related reaction (4% of patients treated with KISUNLA compared to no patient on placebo).

Table 7 shows adverse reactions that were reported in at least 5% of patients treated with KISUNLA and at least 2% more frequently than in patients on placebo in Study 1.

Table 7: Adverse Reactions Reported in at Least 5% of Patients Treated With KISUNLA and at Least 2% Higher Than Placebo in Study 1
Adverse Reaction | KISUNLAa N = 853 % | Placebo N = 874 %
ARIA-H microhemorrhageb | 25 | 11
ARIA-E | 24 | 2
ARIA-H superficial siderosisb | 15 | 3
Headache | 13 | 10
Infusion-related reaction | 9 | 0.5
a Administered as a different titration regimen (700 mg/700 mg/700 mg/1,400 mg) than the currently recommended dosing regimen (350 mg/700 mg/1,050 mg/1,400 mg)
b As assessed by MRI. A participant could have both microhemorrhage and superficial siderosis.

Study 2

In Study 2 (NCT05738486), a total of 842 patients received at least one dose of KISUNLA; 212 patients were randomized to receive KISUNLA Dosing Regimen 2. In Study 2, compared to the rates reported with Dosing Regimen 1, higher rates of hypersensitivity reactions (8% of patients treated with Dosing Regimen 2) and infusion-related reactions (16% of patients treated with Dosing Regimen 2), and a lower rate of ARIA-E (16% of patients treated with Dosing Regimen 2) were observed [see Warnings and Precautions (5.1) and Clinical Studies (14)].

Less Common Adverse Reactions

Hypersensitivity Reactions [see Warnings and Precautions (5.2)]

Hypersensitivity reactions, including anaphylaxis, occurred in 3% of patients treated with KISUNLA compared to 0.7% of patients on placebo in Study 1 and in 8% of patients treated with KISUNLA Dosing Regimen 2 in Study 2.

Intestinal Obstruction and Intestinal Perforation

Serious adverse reactions of intestinal obstruction occurred in three patients (0.4%) treated with KISUNLA compared to no patients on placebo in Study 1 and one patient (0.5%) treated with KISUNLA Dosing Regimen 2 in Study 2. Serious adverse reactions of intestinal perforation occurred in two patients (0.2%) treated with KISUNLA compared to one patient (0.1%) on placebo in Study 1.

Immunogenicity: Anti-Drug Antibody-Associated Adverse Reactions [see Warnings and Precautions (5.2) and Clinical Pharmacology (12.6)]

Infusion-related reactions occurred more frequently in patients treated with KISUNLA who developed anti-drug antibodies (ADAs) compared to patients who did not develop ADAs (Study 1, Dosing Regimen 1: 10% compared to 2%; Study 2, Dosing Regimen 2: 20% compared to 8%).

8 USE IN SPECIFIC POPULATIONS

8.1 Pregnancy

Risk Summary

There are no adequate data on KISUNLA use in pregnant women to evaluate for a drug-associated risk of major birth defects, miscarriage, or other adverse maternal or fetal outcomes. No animal studies have been conducted to assess the potential reproductive or developmental toxicity of KISUNLA.

In the U.S. general population, the estimated background risk of major birth defects and miscarriage in clinically recognized pregnancies is 2 to 4% and 15 to 20%, respectively. The background risk of major birth defects and miscarriage for the indicated population is unknown.

8.2 Lactation

Risk Summary

There are no data on the presence of donanemab-azbt in human milk, the effects on the breastfed infant, or the effects of the drug on milk production. Published data from other monoclonal antibodies generally indicate low passage of monoclonal antibodies into human milk and limited systemic exposure in the breastfed infant. The effects of this limited exposure are unknown. The developmental and health benefits of breastfeeding should be considered along with the mother's clinical need for KISUNLA and any potential adverse effects on the breastfed infant from KISUNLA or from the underlying maternal condition.

8.4 Pediatric Use

Safety and effectiveness in pediatric patients have not been established.

8.5 Geriatric Use

In Study 1, the age of patients exposed to KISUNLA ranged from 59 to 86 years, with a mean age of 73 years; 90% were 65 years and older, and 41% were 75 years and older. No overall differences in safety or effectiveness of KISUNLA have been observed between patients 65 years of age and older and younger adult patients.

In Study 2, the range of patients exposed to KISUNLA ranged from 59 to 85 years, with mean age of 74 years; 93% were 65 years and older, 55% were 75 years and older. Study 2 did not include a sufficient number of younger adult patients to determine if patients 65 years of age and older respond differently than younger adult patients.

11 DESCRIPTION

Donanemab-azbt is a humanized immunoglobulin gamma 1 (IgG1) monoclonal antibody directed against insoluble N-truncated pyroglutamate amyloid beta, and is expressed in a Chinese hamster ovary cell line. Donanemab-azbt has an approximate molecular weight of 145 kDa.

KISUNLA (donanemab-azbt) injection is a sterile, preservative-free, clear to opalescent, colorless to slightly yellow to slightly brown solution for intravenous infusion after dilution. KISUNLA is supplied in single-dose vials available in a concentration of 350 mg/20 mL (17.5 mg/mL).

Each mL of solution contains 17.5 mg donanemab-azbt, anhydrous citric acid (0.32 mg), polysorbate 80 (0.20 mg), sodium citrate (2.15 mg), sucrose (80 mg), and Water for Injection, USP, at a pH of 5.5 to 6.5.

12 CLINICAL PHARMACOLOGY

12.1 Mechanism of Action

Donanemab-azbt is a humanized immunoglobulin gamma 1 (IgG1) monoclonal antibody directed against insoluble N-truncated pyroglutamate amyloid beta. The accumulation of amyloid beta plaques in the brain is a defining pathophysiological feature of Alzheimer's disease. Donanemab-azbt reduces amyloid beta plaques, as evaluated in Study 1 [see Clinical Studies (14)].

12.2 Pharmacodynamics

Effect of KISUNLA on Amyloid Beta Pathology

The effect of KISUNLA on amyloid beta plaque levels in the brain was evaluated using amyloid Positron Emission Tomography (PET) imaging (^18F-florbetapir tracer). The PET signal was quantified using the Standard Uptake Value Ratio (SUVR) method to estimate brain levels of amyloid beta plaque in composites of brain areas expected to be widely affected by Alzheimer's disease pathology (precuneus, frontal, anterior cingulate, posterior cingulate, parietal, and temporal cortices), compared to a brain region expected to be spared of such pathology (cerebellum). Results of amyloid PET were also expressed on the Centiloid scale.

In Study 1 [see Clinical Studies (14)], KISUNLA administered at Dosing Regimen 1 reduced amyloid beta plaque levels in the brain in a time-dependent manner, starting at Week 24, and continuing through Week 76 (p<0.0001), compared to placebo (see Figure 1 and Table 7). In Study 2, Dosing Regimen 2 resulted in similar amyloid plaque reduction compared to Dosing Regimen 1 at Week 24. In clinical pharmacology studies, KISUNLA demonstrated a dose- and time-dependent reduction in amyloid beta plaque, with the decrease observed starting at Week 12.

Figure 1: Reduction in Brain Amyloid Beta Plaque (Change from Baseline) on Amyloid Beta PET Imaging Composite (SUVR and Centiloids) in Study 1a

a ****p<0.0001.

During an off-treatment period, amyloid PET values began to increase with a median rate of 2.80 Centiloids/year.

Effect of KISUNLA on Tau Pathophysiology

A reduction in plasma p-tau217 was observed with KISUNLA compared to placebo in Study 1 (see Table 8).

Table 8: Biomarker Results of KISUNLA in Study 1 (AACI)
Biomarker Endpoint at Week 76 | KISUNLA | Placebo
Amyloid Beta PET SUVR | N = 712 | N = 754
Mean baseline | 1.53 | 1.52
Adjusted mean change from baseline | -0.47 | -0.00
Difference from placebo | -0.47, p<0.0001
Amyloid Beta PET Centiloid | N = 765 | N = 812
Mean baseline | 104.0 | 101.8
Adjusted mean change from baseline | -87.0 | -0.7
Difference from placebo | -86.4, p<0.0001
Plasma p-tau217 (log10 transformed) a | N = 758 | N = 786
Mean baseline | 0.67 | 0.66
Adjusted mean change from baseline | -0.19 | 0.03
Difference from placebo | -0.22, p<0.0001
N is the number of patients with baseline value.
a Results should be interpreted with caution due to the uncertainties in bioanalysis.

Exposure-Response Relationships

Model based exposure-response analyses for Study 1 demonstrated that exposures to donanemab-azbt were associated with a reduction in clinical decline on iADRS and CDR-SB. An association between reduction in amyloid beta plaque from baseline and clinical decline on iADRS and CDR-SB was also observed.

12.3 Pharmacokinetics

The pharmacokinetics (PK) of KISUNLA were characterized using a population PK analysis with concentration data collected from 2131 patients with Alzheimer's disease who received KISUNLA in single or multiple doses. Accumulation of <1.3-fold occurs with every-4-week dosing. Steady-state exposures, which were similar from Dosing Regimens 1 and 2, are achieved after a single dose. In single doses from 350 to 2800 mg (~2 times the approved recommended dosage of 1,400 mg), and multiple 350 to 1,400 mg doses, exposures (Cmax and AUC) increased proportionally.

Distribution

The central volume of distribution is 3.36 L.

Elimination

KISUNLA is expected to be degraded by proteolytic enzymes in the same manner as endogenous IgG. The mean terminal half-life of donanemab-azbt is approximately 12.1 days. Donanemab-azbt clearance is 0.0255 L/h.

Specific Populations

Age, sex, or race were not found to affect the pharmacokinetics of donanemab-azbt. While body weight was found to influence both clearance and volume of distribution, the resulting changes were not clinically significant.

Patients with Renal or Hepatic Impairment

No clinical studies were conducted to evaluate the pharmacokinetics of donanemab-azbt in patients with renal or hepatic impairment. Donanemab-azbt is degraded by proteolytic enzymes and is not expected to undergo renal elimination or metabolism by hepatic enzymes.

12.6 Immunogenicity

The observed incidence of anti-drug antibodies (ADA) is highly dependent on the sensitivity and specificity of the assay. Differences in assay methods preclude meaningful comparisons of the incidence of ADA in the studies described below with the incidence of ADAs in other studies, including those of donanemab-azbt or of other donanemab products.

In up to 18 months of treatment in Study 1 [see Clinical Studies (14)], 87% (691/792) of patients receiving KISUNLA Dosing Regimen 1 developed anti-donanemab-azbt antibodies, and of those, 100% had neutralizing antibodies. In up to 12 months of treatment in Study 2, 87% (176/202) of patients receiving KISUNLA Dosing Regimen 2 developed anti-donanemab-azbt antibodies, and of those, 100% had neutralizing antibodies.

Anti-donanemab-azbt antibody formation was associated with a higher incidence of infusion-related reactions compared to placebo [see Adverse Reactions (6.1)].

Anti-Drug Antibody Effects on Pharmacokinetics and Pharmacodynamics

The presence of anti-donanemab-azbt antibodies increased donanemab-azbt clearance. Among patients treated with KISUNLA in the placebo-controlled studies who developed anti-donanemab-azbt antibodies, mean donanemab-azbt serum trough concentrations at various time points were lower compared to patients who had not developed anti-donanemab-azbt antibodies. Patients with high ADA titers showed less reduction in amyloid plaque compared to patients with low ADA titers. However, there was no identified clinically significant effect of anti-donanemab-azbt antibodies on the effectiveness of KISUNLA over the treatment duration of 18 months.

13 NONCLINICAL TOXICOLOGY

13.1 Carcinogenesis, Mutagenesis, Impairment of Fertility

Carcinogenesis

Carcinogenicity studies have not been conducted.

Mutagenesis

Genotoxicity studies have not been conducted.

Impairment of Fertility

No studies in animals have been conducted to assess the effects of donanemab-azbt on male or female fertility.

14 CLINICAL STUDIES

The effectiveness of KISUNLA for the treatment of Alzheimer's disease was established by Study 1, which assessed Dosing Regimen 1 (700 mg every 4 weeks for the first 3 doses, and then 1,400 mg every 4 weeks). Study 2 was conducted to assess different titration regimens, including Dosing Regimen 2 (doses every 4 weeks with 350 mg the first infusion, 700 mg the second infusion, 1,050 mg the third infusion, and then 1,400 mg every 4 weeks) that demonstrated comparable pharmacodynamic effects on amyloid plaque reduction with a reduced incidence of ARIA-related events compared to Dosing Regimen 1 [see Dosage and Administration (2.2), Warnings and Precautions (5.1), Clinical Pharmacology (12.2)].

Study 1

The efficacy of KISUNLA was evaluated in a double-blind, placebo-controlled, parallel-group study (Study 1, NCT04437511) in patients with Alzheimer's disease (patients with confirmed presence of amyloid pathology and mild cognitive impairment or mild dementia stage of disease, consistent with Stage 3 and Stage 4 Alzheimer's disease). Patients were enrolled with a Mini-Mental State Examination (MMSE) score of ≥20 and ≤28 and had a progressive change in memory function for at least 6 months. Patients were included in the study based on visual assessment of tau PET imaging with flortaucipir and standardized uptake value ratio (SUVR). Patients were enrolled with or without concomitant approved therapies (cholinesterase inhibitors and the N-methyl-D-aspartate antagonist memantine) for Alzheimer's disease. Patients could enroll in an optional, long-term extension.

In Study 1, 1736 patients were randomized 1:1 to receive 700 mg of KISUNLA Dosing Regimen 1 (N = 860) or placebo (N = 876) for a total of up to 72 weeks. The treatment was switched to placebo based on amyloid PET levels measured at Week 24, Week 52, and Week 76. If the amyloid plaque level was <11 Centiloids on a single PET scan or 11 to <25 Centiloids on 2 consecutive PET scans, the patient was eligible to be switched to placebo.

Additionally, dose adjustments were allowed for treatment-emergent ARIA or symptoms that then showed ARIA-E or ARIA-H on MRI.

At baseline, mean age was 73 years, with a range of 59 to 86 years. Of the total number of patients randomized, 68% had low/medium tau level and 32% had high tau level; 71% were ApoE ε4 carriers and 29% were ApoE ε4 noncarriers. Fifty-seven percent of patients were female, 91% were White, 6% were Asian, 4% were Hispanic or Latino, and 2% were Black or African American.

The primary efficacy endpoint was change in the integrated Alzheimer's Disease Rating Scale (iADRS) score from baseline to 76 weeks. The iADRS is a combination of two scores: the Alzheimer's Disease Assessment Scale-Cognitive subscale (ADAS-Cog13) and the Alzheimer's Disease Cooperative Study – instrumental Activities of Daily Living (ADCS-iADL) scale. The total score ranges from 0 to 144, with lower scores reflecting worse cognitive and functional performance. Other efficacy endpoints included Clinical Dementia Rating Scale – Sum of Boxes (CDR-SB), ADAS-Cog13, and ADCS-iADL.

There were two primary analysis populations based on tau PET imaging with flortaucipir: 1) low/medium tau level population (defined by visual assessment and SUVR of ≥1.10 and ≤1.46), and 2) combined population of low/medium plus high tau (defined by visual assessment and SUVR >1.46) population.

Patients treated with KISUNLA demonstrated a statistically significant reduction in clinical decline on iADRS compared to placebo at Week 76 in the combined population (2.92, p<0.0001) and the low/medium tau population (3.25, p<0.0001).

Patients treated with KISUNLA demonstrated a statistically significant reduction in clinical decline on CDR-SB compared to placebo at Week 76 in the combined population (-0.70, p<0.0001) (see Figure 2 and Table 8). There were also statistically significant differences (p<0.001) between treatment groups as measured by ADAS-Cog13 and ADCS-iADL at Week 76 (see Table 9).

Dosing was continued or stopped in response to observed effects on amyloid imaging. The percentages of patients eligible for switch to placebo based on amyloid PET levels at Week 24, Week 52, and Week 76 timepoints were 17%, 47%, and 69%, respectively. Amyloid PET values may increase after treatment with donanemab is stopped [see Clinical Pharmacology (12.2)]. There is no data beyond the 76-week duration of Study 1 to guide whether additional dosing with KISUNLA may be needed for longer-term clinical benefit.

Figure 2: CDR-SB Change From Baseline in Combined Population Through 76 Weeks in Study 1 a

a ****p<0.0001 versus placebo.

Table 9: Efficacy Analysis Results in Combined Population at Week 76a in Study 1
Clinical Endpoints | KISUNLA (N = 860) | Placebo (N = 876)
CDR-SBb
Mean baseline | 3.92 | 3.89
Adjusted mean change from baseline | 1.72 | 2.42
Difference from placebo (%)d | -0.70 (29%) p<0.0001 | --
ADAS-Cog 13 c
Mean baseline | 28.53 | 29.16
Adjusted mean change from baseline | 5.46 | 6.79
Difference from placebo (%)d | -1.33 (20%) p=0.0006 | --
ADCS-iADLc
Mean baseline | 47.96 | 47.98
Adjusted mean change from baseline | -4.42 | -6.13
Difference from placebo (%)d | 1.70 (28%) p=0.0001 | --
a Abbreviations: ADAS-Cog13 = Alzheimer's Disease Assessment Scale – 13-item Cognitive Subscale; ADCS-iADL = Alzheimer's Disease Cooperative Study – instrumental Activities of Daily Living subscale; CDR-SB = Clinical Dementia Rating Scale – Sum of Boxes; NCS2 = natural cubic spline with 2 degrees of freedom; MMRM = mixed model for repeated measures.
b Assessed using MMRM analysis.
c Assessed using NCS2 analysis.
d Percent slowing of decline relative to placebo: difference of adjusted mean change from baseline between treatment groups divided by adjusted mean change from baseline of placebo group at Week 76.

Study 2

Study 2 (NCT05738486) was a randomized, double-blind study investigating the effect of different KISUNLA dosing regimens on ARIA-E and change from baseline in amyloid in adults with Alzheimer's disease (patients with confirmed amyloid pathology and mild cognitive impairment or mild dementia stage of disease). Inclusion and exclusion criteria were the same as Study 1 except that tau PET was not an inclusion criterion. Patients were randomized to receive Dosing Regimen 1 (N=207), or one of three alternative regimens, including Dosing Regimen 2 (N=212) in a 1:1:1:1 ratio [see Dosing and Administration (2.2)]. The treatment period was up to 72 weeks, and treatment stopping criteria based on amyloid PET were the same as Study 1.

Of the 212 patients receiving Dosing Regimen 2, the mean age was 74 years. Fifty-nine percent were female, 91% were White, 6.6% were Black or African American, 5.2% were Hispanic or Latino, and 1.4% were Asian. Overall, 65% of these patients were ApoE ε4 carriers, with 55% heterozygotes and 10% homozygotes, and 36% were noncarriers.

The primary endpoint of the study was the proportion of patients with any occurrence of ARIA-E. The results showed that patients receiving Dosing Regimen 2 had less incidence of ARIA-E by Week 52 compared with patients receiving Dosing Regimen 1 (see Table 10).

ARIA-E occurred at a higher incidence in ApoE ε4 homozygotes, compared to heterozygotes, with the lowest incidence in noncarriers. The small number of events and limited exposure in the ApoE ε4 subgroups limit definitive conclusions about the risk of ARIA-E.

Table 10: Cumulative Incidence of ARIA-E and ARIA-H in 52 Weeks, Overall and by ApoE e4 Genotype, in Study 2
 | Dosing Regimen 1 | Dosing Regimen 2
 | N=207 | N=212
ARIA-E Overall
n (incidence, %) | 50 (24.9) | 33 (16.2)
RD (95% CI) | - | 8.7 (0.8, 16.5)
ARIA-H Overall
n (incidence, %) | 56 (28.1) | 51 (25.2)
RD (95% CI) | - | 2.9 (-5.8, 11.6)
Homozygotes, N | 21 | 21
ARIA-E
n (incidence^1, %) | 12 (57.1) | 5 (24.4)
RD (95% CI) | - | 32.7 (4.4, 60.9)
ARIA-H
n (incidence^1, %) | 10 (47.6) | 6 (28.6)
RD (95% CI) | - | 19.0 (-9.8, 47.8)
Heterozygotes, N | 112 | 115
ARIA-E
n (incidence^1, %) | 27 (25.0) | 18 (16.4)
RD (95% CI) | - | 8.6 (-2.2, 19.3)
ARIA-H
n (incidence^1, %) | 34 (31.8) | 33 (30.8)
RD (95% CI) | - | 1.0 (-11.5, 13.5)
ApoE noncarriers, N | 72 | 75
ARIA-E
n (incidence^1, %) | 11 (15.6) | 10 (13.8)
RD (95% CI) | - | 1.8 (-9.8, 13.5)
ARIA-H
n (incidence^1, %) | 12 (17.2) | 12 (16.4)
RD (95% CI) | - | 0.8 (-11.5, 13.1)
^1 Kaplan-Meier estimates of cumulative incidence
Abbreviations: CI = confidence interval, RD = risk difference

16 HOW SUPPLIED/STORAGE AND HANDLING

16.1 How Supplied

KISUNLA (donanemab-azbt) injection is a sterile, preservative-free, clear to opalescent, colorless to slightly yellow to slightly brown solution. KISUNLA is supplied in one vial per carton as follows:

350 mg/20 mL (17.5 mg/mL) single-dose vial: NDC 0002-9401-01.

16.2 Storage and Handling

Unopened Vial

- Store refrigerated at 2°C to 8°C (36°F to 46°F).
- Keep the vial in the outer carton to protect from light.
- Do not freeze or shake.
- If refrigeration is not available, may be stored at room temperature (20°C to 25°C [68°F to 77°F]) for up to 3 days.

Diluted Solution

For storage of the diluted infusion solution see Dosage and Administration (2.4).

17 PATIENT COUNSELING INFORMATION

Advise the patient to read the FDA-approved patient labeling (Medication Guide).

Amyloid Related Imaging Abnormalities

Inform patients that KISUNLA may cause Amyloid Related Imaging Abnormalities or “ARIA”. ARIA most commonly presents as temporary swelling in areas of the brain that usually resolves over time. Some people may also have small spots of bleeding in or on the surface of the brain. Inform patients that most people with swelling in areas of the brain do not experience symptoms, however some people may experience symptoms such as headache, confusion, dizziness, vision changes, nausea, aphasia, weakness, or seizure. Instruct patients to notify their healthcare provider immediately if these symptoms occur. Clinical evaluation should be performed, and an MRI may be considered. Inform patients that serious symptoms of ARIA may occur and that ARIA can be fatal. Inform patients that events of intracerebral hemorrhage greater than 1 cm in diameter have been reported infrequently in patients taking KISUNLA, and that use of antithrombotic or thrombolytic medications while taking KISUNLA may increase the risk of bleeding in the brain. Notify patients that their healthcare provider will perform MRI scans to monitor for ARIA [see Warnings and Precautions (5.1)].

Inform patients that although ARIA can occur in any patient treated with KISUNLA, there is an increased risk in patients who are ApoE ε4 homozygotes, and that testing for ApoE ε4 status should be performed prior to initiation of treatment to inform the risk of developing ARIA. Prior to testing, discuss with patients the risk of ARIA across genotypes and the implications of genetic testing results. Inform patients that if testing is not performed, it cannot be determined if they are ApoE ε4 homozygotes and at a higher risk for ARIA.

Inform patients that some symptoms of ARIA can mimic ischemic stroke and that their healthcare providers may need to perform additional testing to determine how to treat those symptoms in patients taking KISUNLA. Advise patients to carry information that they are being treated with KISUNLA.

Patient Registry

Providers should encourage patients to participate in real world data collection (e.g., registries) to help further the understanding of Alzheimer's disease and the impact of Alzheimer's disease treatments. Providers and patients can contact 1-800-LillyRx (1-800-545-5979) for a list of currently enrolling programs.

Hypersensitivity Reactions

Inform patients that KISUNLA may cause hypersensitivity reactions, including anaphylaxis and angioedema, and to contact their healthcare provider immediately if hypersensitivity reactions occur [see Warnings and Precautions (5.2)].

Infusion-Related Reactions

Inform patients that KISUNLA may cause infusion-related reactions, including chills, erythema, nausea, vomiting, difficulty breathing, sweating, headache, chest pain, and high or low blood pressure. Advise patients that symptoms can occur during an infusion or after they leave the infusion center and to contact their healthcare provider if infusion related reactions occur [see Warnings and Precautions (5.3)].

Eli Lilly and Company, Indianapolis, IN 46285, USA

US License No. 1891

Copyright © 2024, 2025, Eli Lilly and Company. All rights reserved.

KIS-0003-USPI-20250722

MEDICATION GUIDE
KISUNLA™ (kih-SUHN-lah)
(donanemab-azbt)
injection, for intravenous use

What is the most important information I should know about KISUNLA?
KISUNLA can cause serious side effects, including:
Amyloid Related Imaging Abnormalities or ARIA. ARIA is a common side effect that does not usually cause any symptoms, but serious symptoms can occur. ARIA can be fatal. It is most commonly seen as temporary swelling in areas of the brain that usually resolves over time. Some people may also have small spots of bleeding in or on the surface of the brain, and infrequently, larger areas of bleeding in the brain can occur. Most people who develop ARIA do not get symptoms; however, some people may have symptoms such as:

- headache
- confusion

- dizziness
- vision changes

- nausea
- seizures

- difficulty walking

Some people have a genetic risk factor (homozygous apolipoprotein E ε4 gene carriers) that may cause an increased risk for ARIA. Talk to your healthcare provider about testing to see if you have this risk factor.
You may be at a higher risk of developing bleeding in the brain if you take medicines to reduce blood clots from forming (antithrombotic medicines) while receiving KISUNLA.
Your healthcare provider will do magnetic resonance imaging (MRI) scans before and during your treatment with KISUNLA to check you for ARIA.
You should carry information that you are receiving KISUNLA which can cause ARIA, and that ARIA symptoms can look like stroke symptoms.
Call your healthcare provider or go to the nearest hospital emergency room right away if you have any of the symptoms listed above.
There are registries that collect information on treatments for Alzheimer's disease. Your healthcare provider can help you become enrolled in these registries. For more information, go to www.kisunla.com or call 1-800-LillyRx (1-800-545-5979).

What is KISUNLA?

- KISUNLA is a prescription medicine used to treat people with Alzheimer's disease.

It is not known if KISUNLA is safe and effective in children.

Do not receive KISUNLA if you:

- have serious allergic reactions to donanemab-azbt or any of the ingredients in KISUNLA. See the end of this Medication Guide for a complete list of ingredients in KISUNLA.

Before receiving KISUNLA, tell your healthcare provider about all of your medical conditions, including if you:

- are pregnant or plan to become pregnant. It is not known if KISUNLA will harm your unborn baby. Tell your healthcare provider if you become pregnant during your treatment with KISUNLA.
- are breastfeeding or plan to breastfeed. It is not known if donanemab-azbt (the active ingredient in KISUNLA) passes into your breast milk. Talk to your healthcare provider about the best way to feed your baby while receiving KISUNLA.

Tell your healthcare provider about all of the medicines you take, including prescription and over-the-counter medicines, vitamins, and herbal supplements. Especially tell your healthcare provider if you take medicines to reduce blood clots from forming (antithrombotic medicines, including aspirin). Ask your healthcare provider for a list of these medications if you are not sure.
Know the medicines you take. Keep a list of them to show your healthcare provider and pharmacist when you get a new medicine.

How will I receive KISUNLA?

- KISUNLA is given by your healthcare provider through a needle placed in your vein (intravenous (IV) infusion) in your arm.
- KISUNLA is given every 4 weeks. Each infusion will last about 30 minutes.
- If you miss an infusion of KISUNLA, you should receive your next dose as soon as possible.

What are the possible side effects of KISUNLA?
KISUNLA can cause serious side effects, including:

- See “What is the most important information I should know about KISUNLA?”
- Serious allergic reactions. Swelling of the face, lips, mouth, or eyelids, difficulty breathing, and hives have happened during a KISUNLA infusion. Tell your healthcare provider if you have any symptoms of a serious allergic reaction during or after KISUNLA infusion.
- Infusion-related reactions. Infusion-related reactions, which can be serious, have happened. If you have an infusion-related reaction, your infusion may be slowed down or stopped. Tell your healthcare provider right away if you get these symptoms during an infusion of KISUNLA:
  - chills
  - irritation of skin
  - nausea
  - vomiting
  - sweating
  - headache
  - chest pain
  - problems breathing

If you have ever had an infusion-related reaction while receiving KISUNLA, your healthcare provider may give you medicines before your KISUNLA infusions to decrease your chance of having an infusion reaction. These medicines may include an antihistamine, acetaminophen, or a steroid.
The most common side effects of KISUNLA include:

- swelling in areas of the brain with or without small spots of bleeding in or on the surface of the brain (ARIA).
- headache.

These are not all the possible side effects of KISUNLA. For more information ask your healthcare provider or pharmacist. Call your doctor for medical advice about side effects. You may report side effects to FDA at 1-800-FDA-1088.

General information about the safe and effective use of KISUNLA
Medicines are sometimes prescribed for purposes other than those listed in this Medication Guide. You can ask your pharmacist or healthcare provider for more information about KISUNLA that is written for health professionals.

What are the ingredients in KISUNLA?
Active ingredient: donanemab-azbt
Inactive ingredients: anhydrous citric acid, polysorbate 80, sodium citrate, sucrose, and Water for Injection, USP
KISUNLA is a trademark of Eli Lilly and Company.
For more information, go to www.kisunla.com or call 1-800-LillyRx (1-800-545-5979).
Eli Lilly and Company, Indianapolis, IN 46285, USA
US License No. 1891
Copyright © 2024, Eli Lilly and Company. All rights reserved.

This Medication Guide has been approved by the U.S. Food and Drug Administration

Issued: 7/2024

KIS-0001-MG-20240702

PACKAGE LABEL – Kisunla 350 mg Vial

Product of Ireland or South Korea

NDC 0002-9401-01

Rx only

kisunlaTM

(donanemab-azbt)

injection

350 mg/20 mL

(17.5 mg/mL)

For Intravenous Infusion Only

Must Dilute Prior to Use

One Single-Dose Vial

Dispense with enclosed Medication Guide

www.kisunla.com

Lilly

Product of Ireland

Product of South Korea